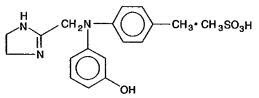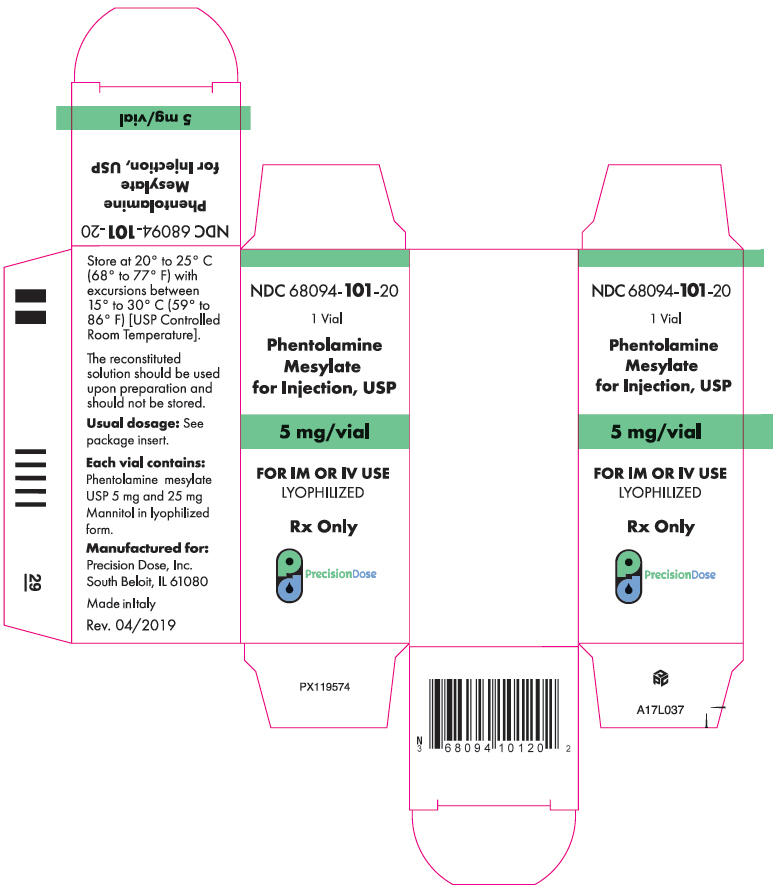 DRUG LABEL: PHENTOLAMINE MESYLATE
NDC: 68094-101 | Form: INJECTION
Manufacturer: Precision Dose Inc.
Category: prescription | Type: HUMAN PRESCRIPTION DRUG LABEL
Date: 20240819

ACTIVE INGREDIENTS: PHENTOLAMINE MESYLATE 5 mg/1 1
INACTIVE INGREDIENTS: MANNITOL 25 mg/1 1

Phentolamine Mesylate for Injection USP, 5mg

DESCRIPTION

Phentolamine Mesylate for Injection, USP is an antihypertensive, available in vials for intravenous and intramuscular administration. Each vial contains phentolamine mesylate, USP, 5 mg, and mannitol USP, 25 mg, in sterile, lyophilized form.

Phentolamine Mesylate, USP is 4,5-dihydro-2-[N-(m-hydroxyphenyl)-N-(p-methylphenyl) amino methyl]-1H- imidazole 1:1 methanesulfonate, and its structural formula is

Phentolamine mesylate, USP is a white or off-white, odorless crystalline powder with a molecular weight of 377.46. Its solutions are acid to litmus. It is freely soluble in water and in alcohol, and slightly soluble in chloroform. It melts at about 178°C.

CLINICAL PHARMACOLOGY

Phentolamine Mesylate for Injection, USP produces an alpha-adrenergic block of relatively short duration. It also has direct, but less marked, positive inotropic and chronotropic effects on cardiac muscle and vasodilator effects on vascular smooth muscle.

Phentolamine Mesylate for Injection, USP has a half-life in the blood of 19 minutes following intravenous administration. Approximately 13% of a single intravenous dose appears in the urine as unchanged drug.

INDICATIONS AND USAGE

Phentolamine Mesylate for Injection, USP is indicated for the prevention or control of hypertensive episodes that may occur in a patient with pheochromocytoma as a result of stress or manipulation during preoperative preparation and surgical excision.

Phentolamine Mesylate for Injection, USP is indicated for the prevention or treatment of dermal necrosis and sloughing following intravenous administration or extravasation of norepinephrine.

Phentolamine Mesylate for Injection, USP is also indicated for the diagnosis of pheochromocytoma by the Phentolamine Mesylate for Injection, USP blocking test.

CONTRAINDICATIONS

Myocardial infarction, history of myocardial infarction, coronary insufficiency, angina or other evidence suggestive of coronary artery disease; hypersensitivity to phentolamine or related compounds.

WARNINGS

Myocardial infarction, cerebrovascular spasm, and cerebrovascular occlusion have been reported to occur following the administration of Phentolamine Mesylate for Injection, USP, usually in association with marked hypotensive episodes.

For screening tests in patients with hypertension, the generally available urinary assay of catecholamines or other biochemical assays have largely replaced the Phentolamine Mesylate for Injection, USP and other pharmacological tests for reasons of accuracy and safety. None of the chemical or pharmacological tests is infallible in the diagnosis of pheochromocytoma. The Phentolamine Mesylate for Injection, USP blocking test is not the procedure of choice and should be reserved for cases in which additional confirmatory evidence is necessary and the relative risks involved in conducting the test have been considered.

PRECAUTIONS

General

Tachycardia and cardiac arrhythmias may occur with the use of Phentolamine Mesylate for Injection, USP or other alpha-adrenergic blocking agents. When possible, administration of cardiac glycosides should be deferred until cardiac rhythm returns to normal.

Drug Interactions

See DOSAGE AND ADMINISTRATION, Diagnosis of pheochromocytoma, Preparation.

Carcinogenesis, Mutagenesis, Impairment of Fertility

Long-term carcinogenicity studies, mutagenicity studies, and fertility studies have not been conducted with Phentolamine Mesylate for Injection, USP .

Pregnancy Category C

Administration of Phentolamine Mesylate for Injection, USP to pregnant rats and mice at oral doses 24-30 times the usual daily human dose (based on a 60-kg human) resulted in slightly decreased growth and slight skeletal immaturity of the fetuses. Immaturity was manifested by increased incidence of incomplete or unossified calcanei and phalangeal nuclei of the hind limb and of incompletely ossified sternebrae. At oral doses 60 times the usual daily human dose (based on a 60-kg human), a slightly lower rate of implantation was found in the rat. Phentolamine Mesylate for Injection, USP did not affect embryonic or fetal development in the rabbit at oral doses 20 times the usual daily human dose (based on a 60-kg human). No teratogenic or embryo toxic effects were observed in the rat, mouse, or rabbit studies.

There are no adequate and well-controlled studies in pregnant women. Phentolamine Mesylate for Injection, USP should be used during pregnancy only if the potential benefit justifies the potential risk to the fetus.

Nursing Mothers

It is not known whether this drug is excreted in human milk. Because many drugs are excreted in human milk and because of the potential for serious adverse reactions in nursing infants from Phentolamine Mesylate for Injection, USP, a decision should be made whether to discontinue nursing or to discontinue the drug, taking into account the importance of the drug to the mother.

Pediatric Use

See DOSAGE AND ADMINISTRATION

ADVERSE REACTIONS

Acute and prolonged hypotensive episodes, tachycardia, and cardiac arrhythmias have been reported. In addition, weakness, dizziness, flushing, orthostatic hypotension, nasal stuffiness, nausea, vomiting, and diarrhea may occur.
To report SUSPECTED ADVERSE REACTIONS, contact Precision Dose Inc. at 1-844-668-3942 or FDA at 1-800-FDA-1088 or www.fda.gov/medwatch.

OVERDOSAGE

Acute Toxicity

No deaths due to acute poisoning with Phentolamine Mesylate for Injection, USP have been reported.
Oral LD50's (mg/kg): mice, 1000; rats, 1250.

Signs and Symptoms

Overdosage with Phentolamine Mesylate for Injection, USP is characterized chiefly by cardiovascular disturbances, such as arrhythmias, tachycardia, hypotension, and possibly shock. In addition, the following might occur: excitation, headache, sweating, pupillary contraction, visual disturbances; nausea, vomiting, diarrhea; hypoglycemia.

Treatment

There is no specific antidote.

A decrease in blood pressure to dangerous levels or other evidence of shock like conditions should be treated vigorously and promptly. The patient's legs should be kept raised and a plasma expander should be administered. If necessary, intravenous infusion of norepinephrine, titrated to maintain blood pressure at the normotensive level, and all available supportive measures should be included. Epinephrine should not be used, since it may cause a paradoxical reduction in blood pressure.

DOSAGE AND ADMINISTRATION

The reconstituted solution should be used upon preparation and should not be stored.
Note: Parenteral drug products should be inspected visually for particulate matter and discoloration prior to administration, whenever solution and container permit.

1. Prevention or control of hypertensive episodes in the patient with pheochromocytoma.

For preoperative reduction of elevated blood pressure, 5 mg of Phentolamine Mesylate for Injection, USP (1mg for children) is injected intravenously or intramuscularly 1 or 2 hours before surgery, and repeated if necessary.

During surgery, Phentolamine Mesylate for Injection, USP (5 mg for adults, 1 mg for children) is administered intravenously as indicated, to help prevent or control paroxysms of hypertension, tachycardia, respiratory depression, convulsions, or other effects of epinephrine intoxication. (Postoperatively, norepinephrine may be given to control the hypotension that commonly follows complete removal of a pheochromocytoma.)

2. Prevention or treatment of dermal necrosis and sloughing following intravenous administration or extravasation of norepinephrine.

For Prevention: 10 mg of Phentolamine Mesylate for Injection, USP is added to each liter of solution containing norepinephrine. The pressor effect of norepinephrine is not affected.

For Treatment: 5-10 mg of Phentolamine Mesylate for Injection, USP in 10 mL of saline is injected into the area of extravasation within 12 hours.

3. Diagnosis of pheochromocytoma — Phentolamine Mesylate for Injection, USP blocking test.

The test is most reliable in detecting pheochromocytoma in patients with sustained hypertension and least reliable in those with paroxysmal hypertension. False-positive tests may occur in patients with hypertension without pheochromocytoma.

a. Intravenous

Preparation

The CONTRAINDICATIONS, WARNINGS, and PRECAUTIONS sections should be reviewed. Sedatives, analgesics, and all other medications except those that might be deemed essential (such as digitalis and insulin) are withheld for at least 24 hours, and preferably 48 -72 hours, prior to the test. Antihypertensive drugs are withheld until blood pressure returns to the untreated, hypertensive level. This test is not performed on a patient who is normotensive.

Procedure

The patient is kept at rest in the supine position throughout the test, preferably in a quiet, darkened room. Injection of Phentolamine Mesylate for Injection, USP is delayed until blood pressure is stabilized, as evidenced by blood pressure readings taken every 10 minutes for at least 30 minutes.

Five milligrams of Phentolamine Mesylate for Injection, USP is dissolved in 1mL of Sterile Water for Injection. The dose for adults is 5 mg; for children, 1 mg.

The syringe needle is inserted into the vein, and injection is delayed until pressor response to venipuncture has subsided.

Phentolamine Mesylate for Injection, USP is injected rapidly. Blood pressure is recorded immediately after injection, at 30-second intervals for the first 3 minutes, and at 60-second intervals for the next 7 minutes.

Interpretation

A positive response, suggestive of pheochromocytoma, is indicated when the blood pressure is reduced more than 35 mmHg systolic and 25 mmHg diastolic. A typical positive response is a reduction in pressure of 60 mmHg systolic and 25 mmHg diastolic. Usually, maximal effect is evident within 2 minutes after injection. A return to preinjection pressure commonly occurs within 15-30 minutes but may occur more rapidly.

If blood pressure decreases to a dangerous level, the patient should be treated as outlined under OVERDOSAGE.

A positive response should always be confirmed by other diagnostic procedures, preferably by measurement of urinary catecholamines or their metabolites.

A negative response is indicated when the blood pressure is elevated, unchanged, or reduced less than 35 mmHg, systolic and 25 mmHg diastolic after injection of Phentolamine Mesylate for Injection, USP. A negative response to this test does not exclude the diagnosis of pheochromocytoma, especially in patients with paroxysmal hypertension in whom the incidence of false-negative responses is high.

b. Intramuscular

If the intramuscular test for pheochromocytoma is preferred, preparation is the same as for the intravenous test. Five milligrams of Phentolamine Mesylate for Injection, USP is then dissolved in 1mL of Sterile Water for Injection. The dose for adults is 5 mg intramuscularly; for children, 3 mg. Blood pressure is recorded every 5 minutes for 30-45 minutes following injection. A positive response is indicated when the blood pressure is reduced 35 mmHg systolic and 25 mmHg diastolic, or more, within 20 minutes following injection.

HOW SUPPLIED

Vials—each containing 5 mg of Phentolamine mesylate, USP, and 25 mg of mannitol, USP, in sterile, lyophilized form.
Trays of 10 with NDC 68094-101-10
Cartons of 1 with NDC 68094-101-20

The reconstituted solution should be used upon preparation and should not be stored.

Store at 20° to 25°C (68° - 77°F) with excursions between 15° to 30°C (59° to 86°F) [USP Controlled Room Temperature]

You can also call Precision Dose Inc. at 1-800-397-9228 or visit www.precisiondose.com.

Distributed by:
Precision Dose, Inc.
South Beloit, IL 61080

Revised: 10/2017

PRINCIPAL DISPLAY PANEL - 5 mg Vial Carton

NDC 68094-101-20

1 Vial

Phentolamine
Mesylate
for Injection, USP

5 mg/vial

FOR IM OR IV USE
LYOPHILIZED

Rx Only

PrecisionDose